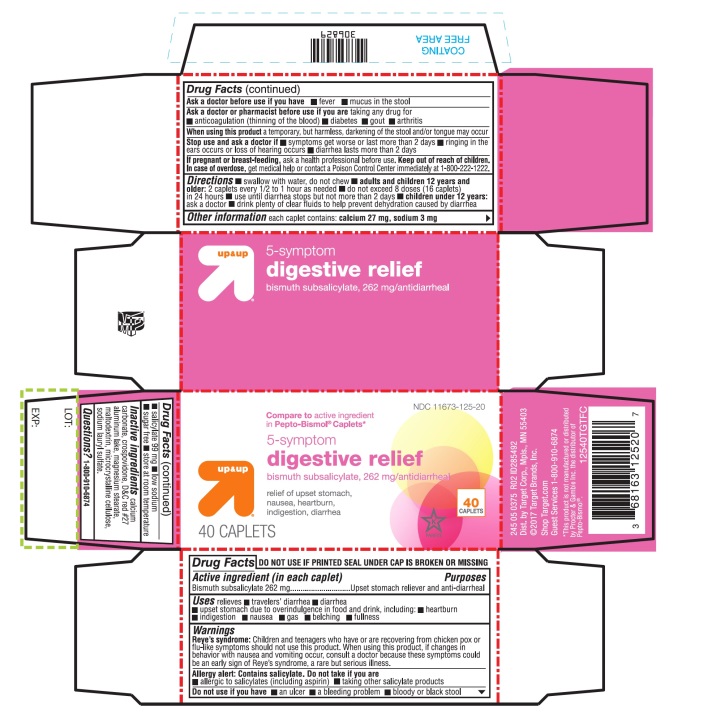 DRUG LABEL: up and up 5-symptom digestive relief
NDC: 11673-125 | Form: TABLET
Manufacturer: Target Corporation
Category: otc | Type: HUMAN OTC DRUG LABEL
Date: 20251104

ACTIVE INGREDIENTS: BISMUTH SUBSALICYLATE 262 mg/1 1
INACTIVE INGREDIENTS: CALCIUM CARBONATE; CROSPOVIDONE (120 .MU.M); D&C RED NO. 27; MAGNESIUM STEARATE; MICROCRYSTALLINE CELLULOSE; SODIUM LAURYL SULFATE

5 Symptom Digestive Relief

Drug Facts

Active ingredient (in each caplet)

Bismuth subsalicylate 262 mg

Purpose

Upset stomach reliever and anti-diarrheal

Uses

relieves

- heartburn
- indigestion
- nausea
- upset stomach
- diarrhea

Warnings

Reye's syndrome

Children and teenagers who have or are recovering from chicken pox or flu-like symptoms should not use this product. When using this product, if changes in behavior with nausea and vomiting occur, consult a doctor because these symptoms could be an early sign of Reye's syndrome, a rare but serious illness.

Allergy alert:

Contains salicylate. Do not take if you are

- allergic to salicylates (including aspirin)
- taking other salicylate products

Do not use ifyou have

- an ulcer
- a bleeding problem
- bloody or black stool

Ask a doctor before use if you have

- fever
- mucus in the stool

Ask a doctor before use if you are taking any drug for

- anticoagulation (thinning of the blood)
- diabetes
- gout
- arthritis

WHEN USING

When using this producta temporary, but harmless, darkening of the stool and/or tongue may occur.

Stop use and ask a doctor if

- symptoms get worse or last more than 2 days
- ringing in the ears occurs or loss of hearing occurs
- diarrhea lasts more than 2 days

PREGNANCY OR BREAST FEEDING

If pregnant or breast feeding,ask a health professional before use.

Keep out of reach of children. In case of overdose, get medical help or contact a Poison Control Center immediately.1-800-222-1222.

Directions

- swallow with water, do not chew
- adults and children 12 years and older:2 caplets every 1/2 to 1 hour as needed
- do not exceed 8 doses (16 caplets) in 24 hours
- use until diarrhea stops but not more than 2 days
- children under 12 years:ask a doctor
- drink plenty of clear fluids to help prevent dehydration caused by diarrhea

Other information

- each caplet contains:calcium 27 mg
- sodium 3 mg
- salicylate 99 mg
- low sodium
- sugar free
- avoid excessive heat (over 104°F or 40°C)

Inactive ingredients

calcium carbonate, crospovidone, D&C red#27 aluminum lake, magnesium stearate, microcrystalline cellulose, sodium lauryl sulfate.

PRINCIPAL DISPLAY PANEL -

NDC 11673-125-20

Compare toactive ingredient in Pepto-Bismol® Caplets*

5- symptom digestive relief

relief of upset stomach, nausea, heartburn, indigestion, diarrhea

40 CAPLETS

*This product is not manufactured or distributed by Procter & Gamble Inc. the distributor of PEPTO-BISMOL®

TAMPER EVIDENT DO NOT USE IF PRINTED SEAL UNDER CAP IS TORN OR MISSING.

245 05 0375 R01 ID285492

Dist.by Target Corp., Mpls ., MN 55403

©2017 Target Brands, Inc.

Shop Target.com

Guest Services 1-800-910-6874